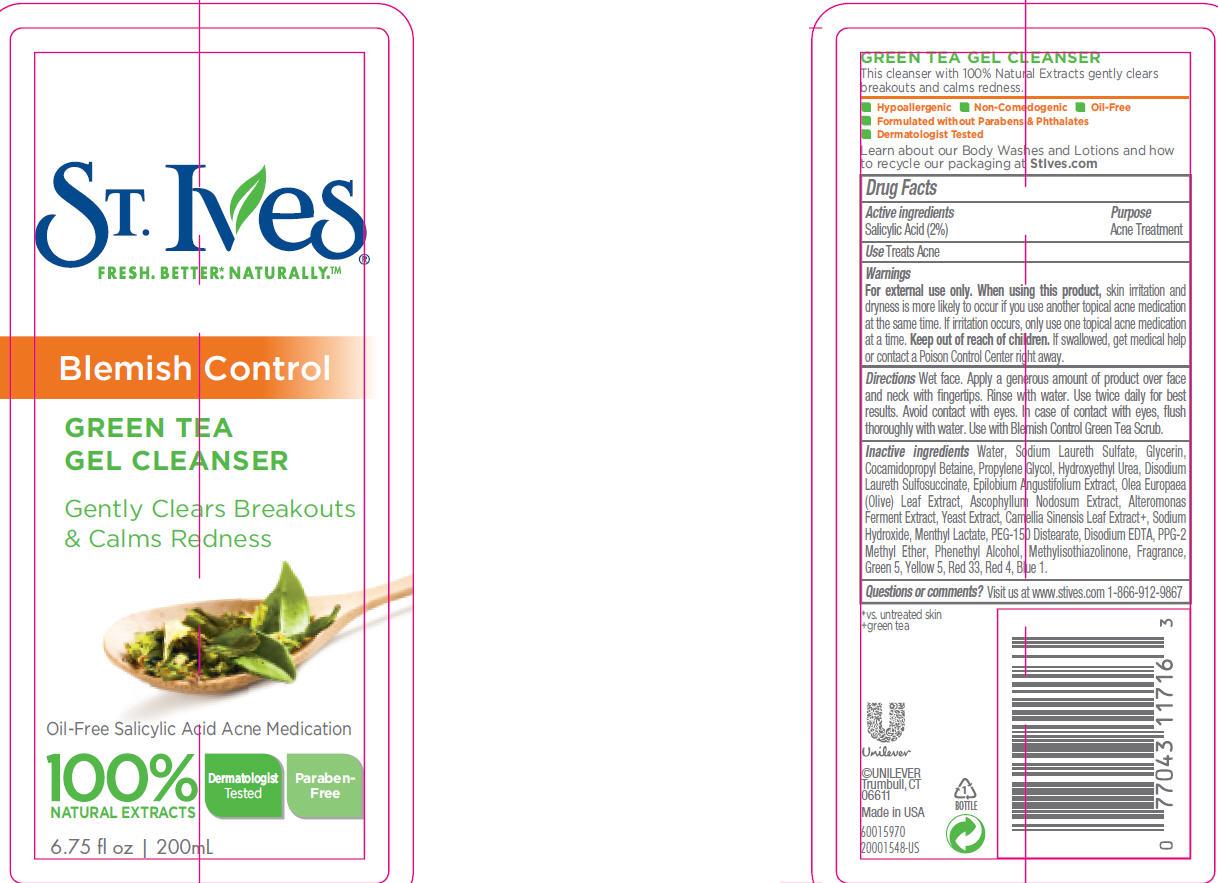 DRUG LABEL: St. Ives
NDC: 64942-1246 | Form: EMULSION
Manufacturer: CONOPCO Inc. d/b/a Unilever
Category: otc | Type: HUMAN OTC DRUG LABEL
Date: 20120308

ACTIVE INGREDIENTS: Salicylic Acid 0.02 mL/1 mL
INACTIVE INGREDIENTS: WATER; SODIUM LAURETH SULFATE; GLYCERIN; COCAMIDOPROPYL BETAINE; PROPYLENE GLYCOL; HYDROXYETHYL UREA; DISODIUM LAURETH SULFOSUCCINATE; SODIUM HYDROXIDE; MENTHYL LACTATE, (-)-; PEG-150 DISTEARATE; EDETATE DISODIUM; PPG-2 METHYL ETHER; PHENYLETHYL ALCOHOL; OLEA EUROPAEA LEAF; ASCOPHYLLUM NODOSUM; METHYLISOTHIAZOLINONE; YEAST; GREEN TEA LEAF; D&C Green No. 5; FD&C YELLOW NO. 5; D&C RED NO. 33; FD&C RED NO. 4; FD&C BLUE NO. 1

St. Ives Green Tea Gel Cleanser

Active ingredient
Salicylic Acid (2%)

Purpose
Acne Treatment

Use
Treats Acne

Warnings
For external use only.

When using this product, skin irritation and dryness is more likely to occur if you use another topical acne medication at the same time. If irritation occurs, only use one topical acne medication at a time.

Keep out of reach of children. If swallowed, get medical help or contact a Poison Control Center right away.

Directions
Wet face. Apply a generous amount of product over face and neck with fingertips. Rinse with water. Use twice daily for best results. Avoid contact with eyes. In case of contact with eyes, flush thoroughly with water. Use with Blemish Control Green Tea Scrub.

Inactive ingredients

Water (Aqua, Eau)

Sodium Laureth Sulfate

Glycerin

Cocamidopropyl Betaine

Propylene Glycol

Salicylic Acid

Hydroxyethyl Urea

Disodium Laureth Sulfosuccinate

Parfum (Fragrance)

Sodium Hydroxide

Menthyl Lactate

PEG-150 Distearate

Disodium EDTA

PPG-2 Methyl Ether

Phenethyl Alcohol

Epilobium Angustifolium Extract

Olea Europaea (Olive) Leaf Extract

Ascophyllum Nodosum Extract

Alteromonas Ferment Extract

Methylisothiazolinone

Yeast Extract

Camellia Sinensis Leaf Extract

CI 61570 (Green 5)

Yellow 5 (CI 19140)

CI 17200 (Red 33)

CI 14700 (Red 4)

CI 42090 (Blue 1)

Questions or comments?
Visit us at www.stives.com 1-866-912-9867

PACKAGE LABEL

PDP